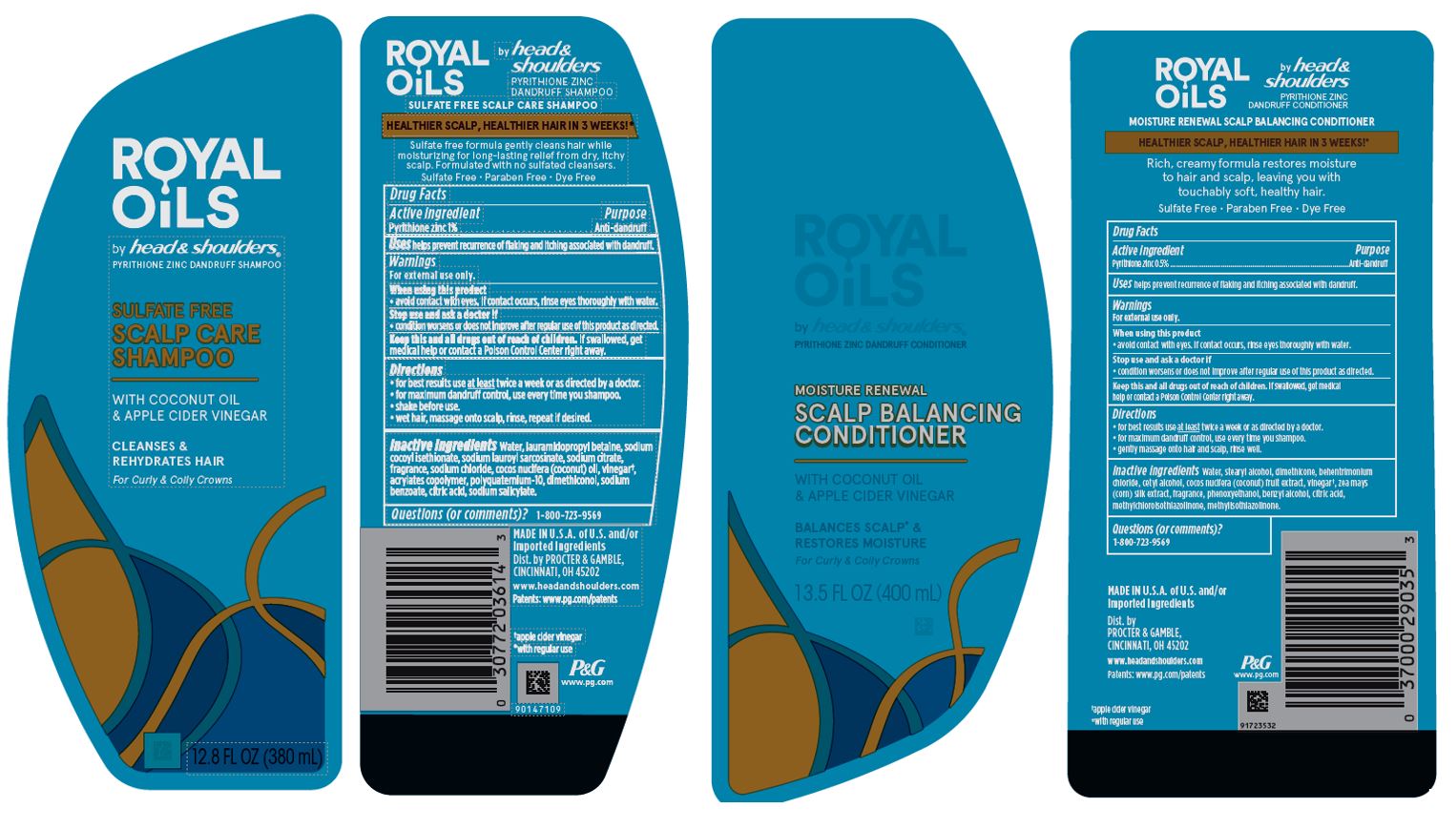 DRUG LABEL: Royal Oils by Head and Shoulders Scalp Care Dual Pack
NDC: 84126-003 | Form: KIT | Route: TOPICAL
Manufacturer: The Procter & Gamble Manufacturing Company
Category: otc | Type: HUMAN OTC DRUG LABEL
Date: 20251218

ACTIVE INGREDIENTS: PYRITHIONE ZINC 1 g/100 mL; PYRITHIONE ZINC 0.5 g/100 mL
INACTIVE INGREDIENTS: CITRIC ACID MONOHYDRATE; SODIUM LAUROYL SARCOSINATE; SODIUM CITRATE; ACETIC ACID; SODIUM SALICYLATE; POLYQUATERNIUM-10 (30000 MPA.S AT 2%); WATER; LAURAMIDOPROPYL BETAINE; SODIUM CHLORIDE; DIMETHICONOL (50000 CST); SODIUM BENZOATE; COCONUT OIL; SODIUM COCOYL ISETHIONATE; STEARYL ALCOHOL; WATER; CETYL ALCOHOL; PHENOXYETHANOL; BENZYL ALCOHOL; METHYLISOTHIAZOLINONE; DIMETHICONE; CITRIC ACID MONOHYDRATE; METHYLCHLOROISOTHIAZOLINONE; COCONUT; CORN SILK; BEHENTRIMONIUM CHLORIDE; ACETIC ACID

Royal Oils by Head and Shoulders® Scalpl Care Kit

ROYAL OILS

by head & shoulders
SULFATE FREE

SCALP CARE

SHAMPOO

Drug Facts

Active ingredient

Pyrithione zinc 1%

Purpose

Anti-dandruff

Uses

helps prevent recurrence of flaking and itching associated with dandruff.

Warnings

For external use only.

When using this product

- avoid contact with eyes. If contact occurs, rinse eyes thoroughly with water.

Stop use and ask a doctor if

- condition worsens or does not improve after regular use of this product as directed.

KEEP OUT OF REACH OF CHILDREN

Keep this and all drugs out of reach of children.

If swallowed, get medical help or contact a Poison Control Center right away.

Directions

- for best results use at least twice a week or as directed by a doctor.
- for maximum dandruff control, use every time you shampoo.
- shake before use.
- wet hair, massage onto scalp, rinse, repeat if desired.

Inactive ingredients

Water, lauramidopropyl betaine, sodium cocoyl isethionate, sodium lauroyl sarcosinate, sodium citrate, fragrance, sodium chloride, cocos nucifera (coconut) oil, vinegar†, acrylates copolymer, polyquaternium-10, dimethiconol, sodium benzoate, citric acid, sodium salicylate.

Questions (or comments)?

1-800-723-9569

ROYAL OILS

by head & shoulders
MOISTURE RENEWAL SCALP BALANCING CONDITIONER

Drug Facts

Active ingredient

Pyrithione zinc 0.5%

Purpose

Anti-dandruff

Uses

helps prevent recurrence of flaking and itching associated with dandruff.

Warnings

For external use only.

When using this product

- avoid contact with eyes. If contact occurs, rinse eyes thoroughly with water.

Stop use and ask a doctor if

- condition worsens or does not improve after regular use of this product as directed.

KEEP OUT OF REACH OF CHILDREN

Keep this and all drugs out of reach of children.

If swallowed, get medical help or contact a Poison Control Center right away.

Directions

- for best results use at least twice a week or as directed by a doctor.
- apply to wet hair after shampooing by gently massaging into hair and scalp, rinse well.

Inactive ingredients

Water, stearyl alcohol, dimethicone, behentrimonium chloride, cetyl alcohol, cocos nucifera (coconut) fruit extract, vinegar†, zea mays (corn) silk extract, fragrance, phenoxyethanol, benzyl alcohol, citric acid, methylchloroisothiazolinone, methylisothiazolinone.

Questions (or comments)?

1-800-723-9569

Dist. by PROCTER & GAMBLE,
CINCINNATI, OH 45202

PRINCIPAL DISPLAY PANEL - Kit

ROYAL OILS

by head & shoulders ®

Shampoo & Conditioner Inside

pyrithione zinc dandruff shampoo

ROYAL OILS

by head & shoulders

SULFATE FREE

SCALP CARE

SHAMPOO

ROYAL OILS

by head & shoulders

pyrithione zinc dandruff conditioner

MOISTURE RENEWAL

SCALP BALANCING

CONDITIONER

1 PYRITHIONE ZINC DANDRUFF

SHAMPOO 12.8 FL OZ (380 mL)

1 PYRITHIONE ZINC DANDRUFF

CONDITIONER 13.5 FL OZ (400 mL)